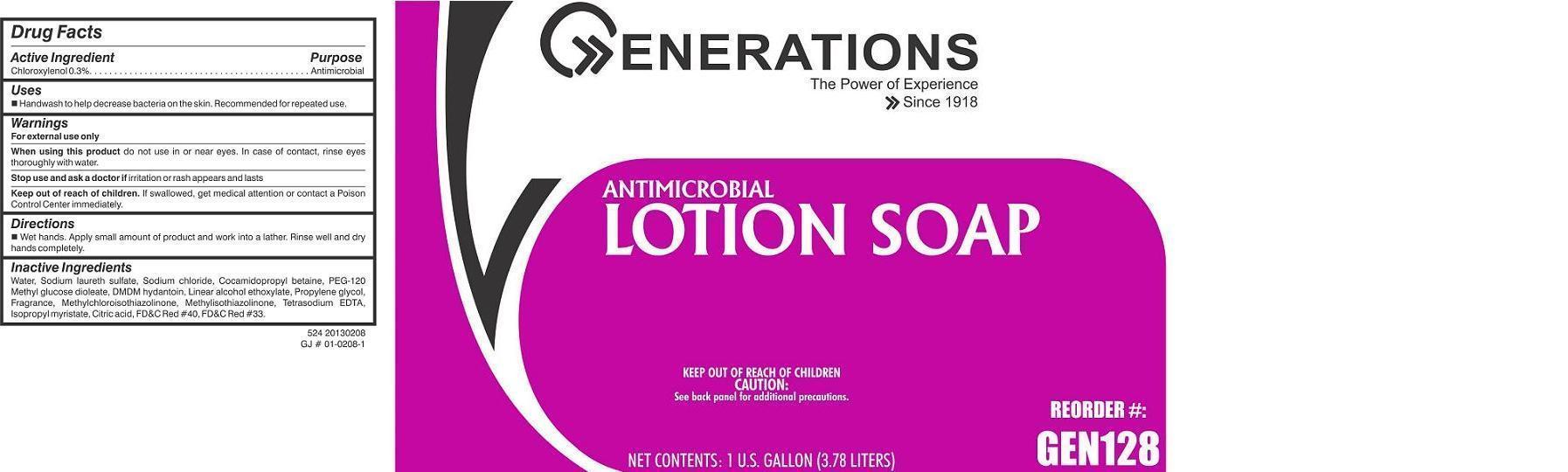 DRUG LABEL: GENERATIONS ANTIMICROBIAL
NDC: 69554-524 | Form: SOAP
Manufacturer: Cole Papers
Category: otc | Type: HUMAN OTC DRUG LABEL
Date: 20150126

ACTIVE INGREDIENTS: CHLOROXYLENOL 3 g/1000 mL
INACTIVE INGREDIENTS: WATER; C9-11 PARETH-6; SODIUM LAURETH SULFATE; PROPYLENE GLYCOL; ISOPROPYL MYRISTATE; METHYLCHLOROISOTHIAZOLINONE; METHYLISOTHIAZOLINONE; COCAMIDOPROPYL BETAINE; DMDM HYDANTOIN; PEG-120 METHYL GLUCOSE DIOLEATE; EDETATE SODIUM; CITRIC ACID MONOHYDRATE; SODIUM CHLORIDE

Active ingredient

Chloroxylenol 0.3% w/w

Purpose

Antimicrobial

Keep out of reach of children

If swallowed, get medical attention or contact a poison control center immediately.

Uses

- Handwash to help decrease bacteria on the skin. Recommended for repeated use.

Warnings

For external use only

When using this product do not use in or near eyes. In case of contact, rinse eyes thoroughly with water.

Stop use and ask a doctor if irritation or rash appears and lasts

Directions

 wet hands  apply small amount of product and work into a lather  rinse well and dry hands completely

Inactive ingredients:

Water, Sodium laureth sulfate, Sodium chloride, Cocamidopropyl betaine, PEG-120 Methyl glucose dioleate, DMDM hydantoin, Linear alcohol ethoxylate, Propylene glycol, Methylchloroisothiazolinone, Methylisothiazolinone, Fragrance, Tetrasodium EDTA, Isopropyl myristate, Citric acid, FD&C Red #40, FD&C Red #33.